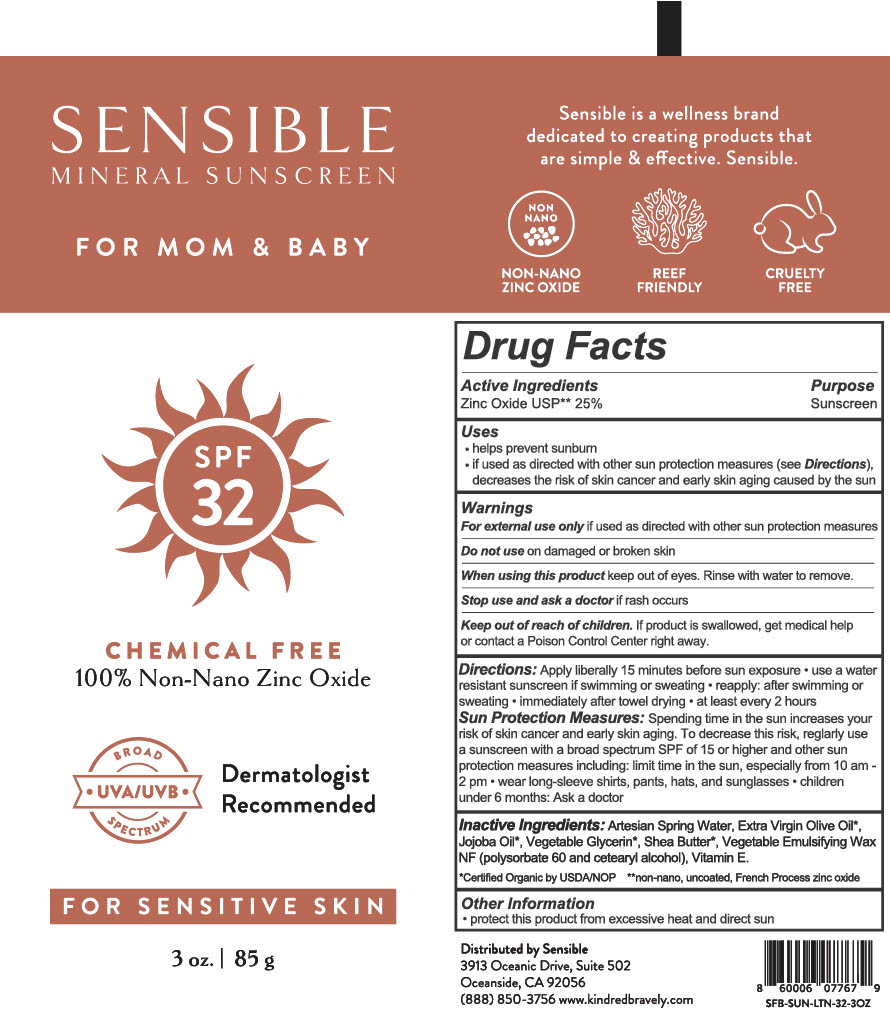 DRUG LABEL: SENSIBLE SPF 32 MINERAL SUNSCREEN
NDC: 82751-101 | Form: CREAM
Manufacturer: Kindred Bravely
Category: otc | Type: HUMAN OTC DRUG LABEL
Date: 20220517

ACTIVE INGREDIENTS: ZINC OXIDE 25 g/100 g
INACTIVE INGREDIENTS: WATER; GLYCERIN; POLYSORBATE 60; CETOSTEARYL ALCOHOL; TOCOPHEROL; SHEA BUTTER; JOJOBA OIL; OLIVE OIL

Active Ingredients

Zinc Oxide 25%

Purpose

Sunscreen

Uses:

- Helps prevent sunburn
- If used as directed with other sun protection measures (see Directions), decreases risk of skin cancer and early skin aging caused by the sun.

Warnings

Warnings

For External Use Only

Do not use on damaged or broken skin

When using this product Keep out of eyes. Rinse with water to remove

Stop use and ask doctor if rash appears

Keep out of reach of children. If

product is swallowed, get medical help

or contact Poison Control Center right

away.

Directions

- Apply generously and evenly to all skin exposed to sun 15 minutes before sun exposure
- Children under 6 months of age: ask a doctor

Sun Protection Measures: Spending time in the sun increases your risk of skin cancer and early skin aging. To decrease this risk, regularly use a sunscreen with a Broad Spectrum SPF value of 15 or higher and other sun protection measures including:

- Limit time in the sun, especially from 10 a.m. - 2 p.m.
- Wear long-sleeved shirts, pants, hats, and sunglasses

Reapply after:

- 40 minutes of swimming or sweating
- Immediately after towel drying
- at least every 2 hours

Other Information: Protect this product from excessive heat and direct sun

Questions or comments? 888-850-3756 or Kindredbravely.com